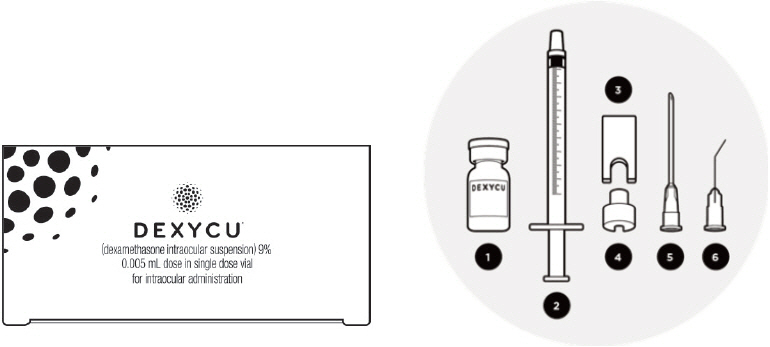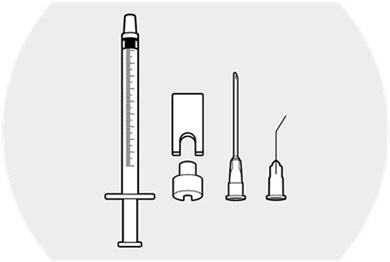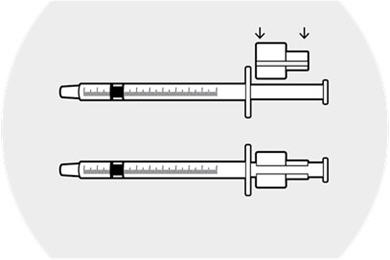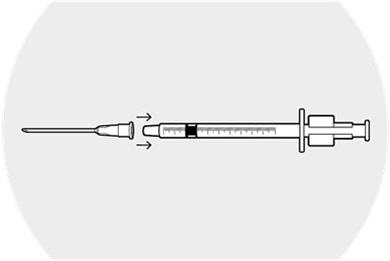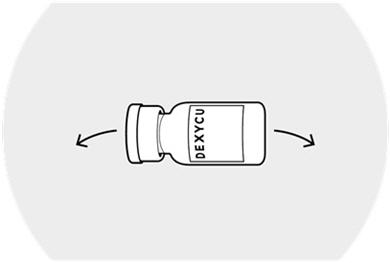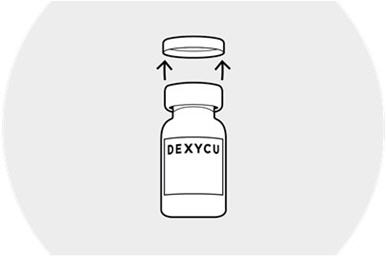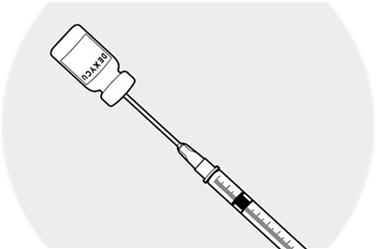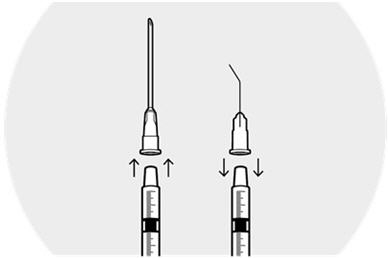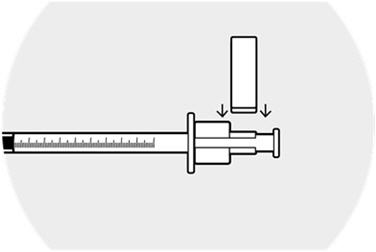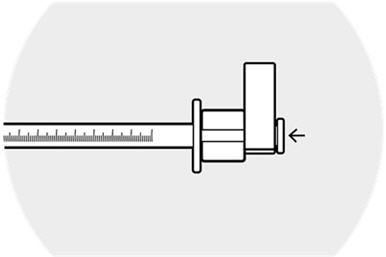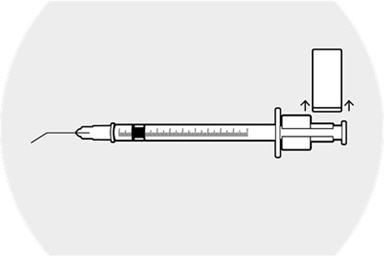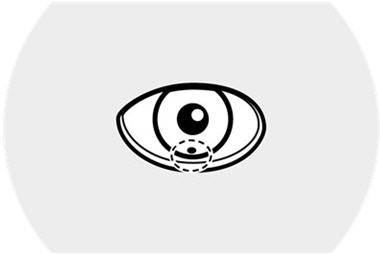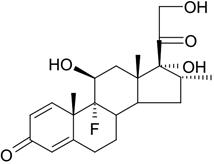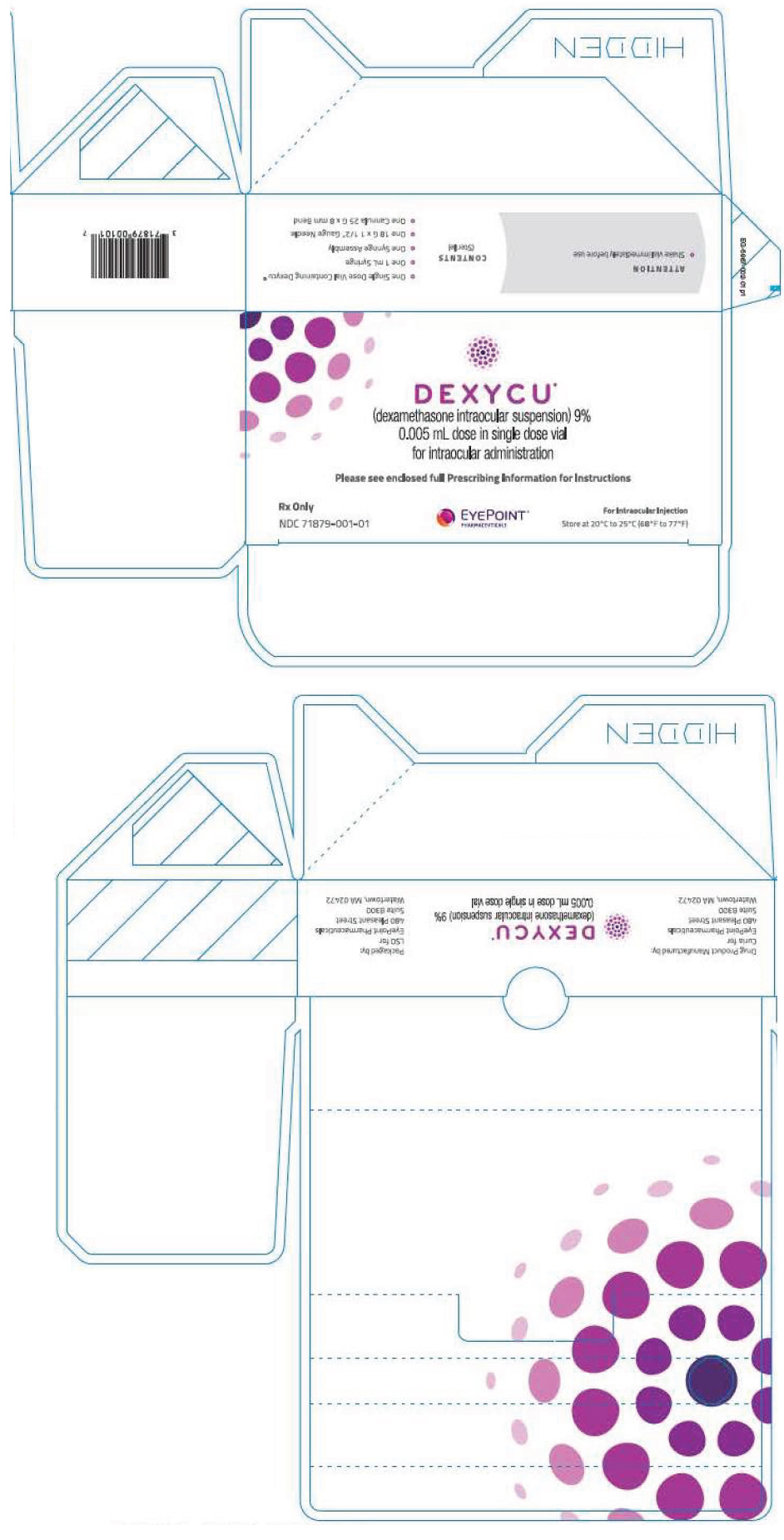 DRUG LABEL: Dexycu
NDC: 71879-001 | Form: INJECTION, SUSPENSION
Manufacturer: EyePoint Pharmaceuticals US, Inc
Category: prescription | Type: HUMAN PRESCRIPTION DRUG LABEL
Date: 20251202

ACTIVE INGREDIENTS: DEXAMETHASONE 517 ug/0.005 mL
INACTIVE INGREDIENTS: ACETYLTRIETHYL CITRATE 5233 ug/0.005 mL; NITROGEN

HIGHLIGHTS OF PRESCRIBING INFORMATION

These highlights do not include all the information needed to use DEXYCU®safely and effectively. See full prescribing information for DEXYCU.
DEXYCU (dexamethasone intraocular suspension) 9%, for intraocular administration
Initial U.S. Approval: 1958

RECENT MAJOR CHANGES

Dosage and Administration (2.2) | 6/2020

1 INDICATIONS AND USAGE

DEXYCU is a corticosteroid indicated for the treatment of postoperative inflammation (1).

2 DOSAGE AND ADMINISTRATION

- For intraocular administration (2).
- Administer 0.005 mL of DEXYCU into the posterior chamber inferiorly behind the iris at the end of ocular surgery (2).

3 DOSAGE FORMS AND STRENGTHS

Intraocular suspension: 9% equivalent to dexamethasone 103.4 mg/mL in a single-dose vial provided in a kit (3).

4 CONTRAINDICATIONS

None (4).

5 WARNINGS AND PRECAUTIONS

- Increase in Intraocular Pressure (IOP): Monitor for increases in IOP (5.1).
- Delayed Healing: Monitor for delayed healing (5.2).
- Infection Exacerbation: Monitor and treat for any exacerbations of bacterial, viral or fungal infections (5.3).
- Cataract Progression: Cataracts may develop or progress in phakic patients (5.4).

6 ADVERSE REACTIONS

In controlled studies, the most common adverse reactions reported by 5-15% of patients were intraocular pressure increased, corneal edema and iritis (6.1).

To report SUSPECTED ADVERSE REACTIONS, contact EyePoint Pharmaceuticals US at 1-833-EYEPOINT (1-833-393-7646) or FDA at 1-800-FDA-1088 or www.fda.gov/medwatch.

FULL PRESCRIBING INFORMATION

1 INDICATIONS AND USAGE

DEXYCU (dexamethasone intraocular suspension) 9% is indicated for the treatment of postoperative inflammation.

2 DOSAGE AND ADMINISTRATION

2.1 Dosing Information

DEXYCU should be administered as a single dose, intraocularly in the posterior chamber at the end of surgery. The dose is 0.005 mL of dexamethasone 9% (equivalent to 517 micrograms).

2.2 Preparation and Administration

Each kit of DEXYCU is for a single administration. After preparation, 0.005 mL will be administered.

The DEXYCU administration kit contains the following items:

1. One glass vial: 0.5 mL of DEXYCU
2. One sterile 1-mL syringe
3. One sterile syringe guide
4. One sterile syringe ring
5. One sterile 18-gauge needle (1½ inches long), plastic cap attached
6. One sterile 25-gauge bent cannula (8 mm long), plastic cap attached

Step 1.
Prepare a sterile field.
Remove the components of the administration kit from their respective pouches:

- syringe
- syringe guide
- syringe ring
- needle
- cannula

Place onto the sterile field.

Step 2.
Withdraw the syringe plunger approximately 1 inch.
Place the syringe ring on the plunger (slit facing the plunger).
Apply slight downward pressure until the syringe ring "snaps" into place.

Step 3.
Place the 18-gauge needle firmly on the syringe.
Remove the cap from the needle.
Depress the plunger completely and then withdraw the plunger to fill the syringe with air.

Step 4.
Mix using a vortex mixer or vigorously shake the vial of DEXYCU sideways for a minimumof 30 seconds.
The suspended drug material must be used immediately after shaking.

Step 5.
Remove the blue plastic flip-cap from the vial and wipe the top of rubber stopper with an alcohol pad.
Invert the vial.

Step 6.
Insert the needle into the vial and inject the air into the vial.
Making sure the needle tip is immersed in the drug material pooled in the neck of the inverted vial, fill the syringe by slowly withdrawing the plunger approximately 0.2 mL.
Remove the needle from the vial and discard the unused portion in the vial.

Step 7.
Remove the needle from the syringe.
Firmly place the cannula on the syringe and remove the plastic cap.
Hold the syringe vertically with the cannula pointing up.
Depress the plunger to expel air bubbles from syringe.

Step 8.
Affix the syringe guide over the syringe ring on the plunger.

Step 9.
Depress the plunger until the syringe guide/ring mechanism comes gently into contact with the flange of the syringe.
Lightly tap/flick the barrel of the syringe to remove any excess drug from the tip of the cannula.
Do not wipe or touch the tip of the cannula to remove excess drug.

Step 10.
Remove the syringe guide, leaving the syringe ring in place.
Caution to not move the plunger.The space between the syringe ring and the top of the plunger is the medication injection volume that will be applied to the patient's eye.
The syringe is now ready for injection.

Step 11.
In a single slow motion, inject 0.005 mL of the drug material behind the iris in the inferior portion of the posterior chamber. If the sphere of administered drug after intraocular injection appears to be larger than 2 mm in diameter, excess drug material may be removed by irrigation and aspiration in the sterile surgical setting
PLEASE NOTE: Some drug material will remain in the syringe after the injection—this is necessary for accurate dosing. Discard unused portion remaining in the syringe after administration.

3 DOSAGE FORMS AND STRENGTHS

DEXYCU contains dexamethasone 9% w/w (103.4 mg/mL) as a sterile suspension for intraocular ophthalmic administration. DEXYCU is provided as a kit for administration of a single dose of 0.005 mL of 9% dexamethasone (equivalent to 517 micrograms of dexamethasone).

4 CONTRAINDICATIONS

None.

5 WARNINGS AND PRECAUTIONS

5.1 Increase in Intraocular Pressure

Prolonged use of corticosteroids including DEXYCU may result in glaucoma with damage to the optic nerve, defects in visual acuity and fields of vision. Steroids should be used with caution in the presence of glaucoma.

5.2 Delayed Healing

The use of steroids after cataract surgery may delay healing and increase the incidence of bleb formation. In those diseases causing thinning of the cornea or sclera, perforations have been known to occur with the use of corticosteroids.

5.3 Exacerbation of Infection

The use of DEXYCU, as with other ophthalmic corticosteroids, is not recommended in the presence of most active viral diseases of the cornea and conjunctiva including epithelial herpes simplex keratitis (dendritic keratitis), vaccinia, and varicella, and also in mycobacterial infection of the eye and fungal disease of ocular structures.

Employment of a corticosteroid medication in the treatment of patients with a history of herpes simplex requires caution. Use of ocular steroids may prolong the course and may exacerbate the severity of many viral infections of the eye (including herpes simplex). Fungal infections of the cornea are particularly prone to develop coincidentally with long-term local steroid application. Fungus invasion must be considered in any persistent corneal ulceration where a steroid has been used or is in use. Fungal culture should be taken when appropriate.

Prolonged use of corticosteroids may suppress the host response and thus increase the hazard of secondary ocular infections. In acute purulent conditions, steroids may mask infection or enhance existing infection.

5.4 Cataract Progression

The use of corticosteroids in phakic individuals may promote the development of posterior subcapsular cataracts.

6 ADVERSE REACTIONS

The following adverse reactions are described elsewhere in the labeling:

- Increase in Intraocular Pressure [see Warnings and Precautions (5.1)]
- Delayed Healing [see Warnings and Precautions (5.2)]
- Infection Exacerbation [see Warnings and Precautions (5.3)]
- Cataract Progression [see Warnings and Precautions (5.4)]

6.1 Clinical Trials Experience

Because clinical trials are conducted under widely varying conditions, adverse reaction rates observed in the clinical studies of a drug cannot be directly compared to rates in the clinical trials of another drug and may not reflect the rates observed in practice.

The following adverse events rates are derived from three clinical trials in which 339 patients received the 517 microgram dose of DEXYCU. The most commonly reported adverse reactions occurred in 5-15% of subjects and included increases in intraocular pressure, corneal edema and iritis. Other ocular adverse reactions occurring in 1-5% of subjects included, corneal endothelial cell loss, blepharitis, eye pain, cystoid macular edema, dry eye, ocular inflammation, posterior capsule opacification, blurred vision, reduced visual acuity, vitreous floaters, foreign body sensation, photophobia, and vitreous detachment.

8 USE IN SPECIFIC POPULATIONS

8.1 Pregnancy

Risk Summary

There are no adequate and well-controlled studies of DEXYCU (dexamethasone intraocular suspension) 9% in pregnant women. Topical ocular administration of dexamethasone in mice and rabbits during the period of organogenesis produced cleft palate and embryofetal death in mice and malformations of abdominal wall/intestines and kidneys in rabbits at doses 7 and 5 times higher than the injected recommended human ophthalmic dose (RHOD) of DEXYCU (517 micrograms dexamethasone), respectively [see Data] .

In the US general population the estimated background risk of major birth defects and miscarriage in clinically recognized pregnancies is 2 to 4% and 15 to 20%, respectively.

Data

Animal Data

Topical ocular administration of 0.15% dexamethasone (0.75 mg/kg/day) on gestational days 10 to 13 produced embryofetal lethality and a high incidence of cleft palate in mice. A dose of 0.75 mg/kg/day in the mouse is approximately 7-times the injected RHOD of DEXYCU, on a mg/m^2basis. In rabbits, topical ocular administration of 0.1% dexamethasone throughout organogenesis (0.20 mg/kg/day on gestational day 6, followed by 0.13 mg/kg/day on gestational days 7 – 18) produced intestinal anomalies, intestinal aplasia, gastroschisis and hypoplastic kidneys. A dose of 0.13 mg/kg/day in the rabbit is approximately 5-times the injected RHOD of DEXYCU, on a mg/m^2basis. A no-observed-adverse-effect-level (NOAEL) was not identified in the mouse or rabbit studies.

8.2 Lactation

Risk Summary

Systemically administered corticosteroids are present in human milk and can suppress growth, interfere with endogenous corticosteroid production, or cause other unwanted effects. There is no information regarding the presence of injected DEXYCU in human milk, the effects on breastfed infants, or the effects on milk production to inform risk of DEXYCU to an infant during lactation. The developmental and health benefits of breastfeeding should be considered, along with the mother's clinical need for DEXYCU and any potential adverse effects on the breastfed child from DEXYCU.

8.4 Pediatric Use

Safety and effectiveness of DEXYCU in pediatric patients have not been established.

8.5 Geriatric Use

No overall differences in safety or effectiveness have been observed between older and younger patients.

11 DESCRIPTION

DEXYCU (dexamethasone intraocular suspension) 9% is a corticosteroid, sterile, white to off-white opaque suspension for intraocular administration. Each vial of DEXYCU contains 0.5 mL of 9% w/w dexamethasone suspension equivalent to 51.7 mg of dexamethasone. The inactive ingredient is acetyl triethyl citrate. DEXYCU does not contain an antimicrobial preservative.

The chemical name of dexamethasone is pregna-1,4-diene-3,20-dione, 9-fluoro-11,17,21-trihydroxy-16-methyl-, (11β,16α)-. It has a molecular formula of C22H29FO5and a molecular weight of 392.46 grams per mole. Its structural formula is:

12 CLINICAL PHARMACOLOGY

12.1 Mechanism of Action

Dexamethasone is a corticosteroid. Corticosteroids have been shown to suppress inflammation by inhibiting multiple inflammatory cytokines resulting in decreased edema, fibrin deposition, capillary leakage and migration of inflammatory cells.

12.3 Pharmacokinetics

Systemic exposure to dexamethasone was evaluated in a subgroup of patients enrolled in two studies (n=25 for the first study and n=13 for the second study). The patients received a single intraocular injection of DEXYCU containing 342 mcg or 517 mcg of dexamethasone at the end of cataract surgery and blood samples were collected prior to surgery and at several time points post-surgery between Day 1 and up to Day 30. In the first study, the dexamethasone plasma concentrations on post-surgery Day 1 ranged from 0.09 to 0.86 ng/mL and from 0.07 to 1.16 ng/mL following administration of DEXYCU 342 mcg and 517 mcg, respectively. In the second study, dexamethasone plasma concentrations on post-surgery Day 1 ranged from 0.349 to 2.79 ng/mL following administration of DEXYCU 517 mcg. In both the studies, dexamethasone plasma concentrations declined over time and very few patients had quantifiable dexamethasone plasma concentrations at the final time point of sampling (Day 15 or Day 30).

13 NONCLINICAL TOXICOLOGY

13.1 Carcinogenesis, Mutagenesis, Impairment of Fertility

Animal studies have not been conducted to determine whether DEXYCU has the potential for carcinogenesis or mutagenesis. Fertility studies have not been conducted in animals.

14 CLINICAL STUDIES

Clinical efficacy was evaluated in a randomized, double-masked, placebo-controlled trial (NCT02006888) in which subjects received either DEXYCU or placebo (vehicle). A dose of 5 microliters of DEXYCU (equivalent to 517 micrograms of dexamethasone), a dose equivalent to 342 micrograms of dexamethasone or vehicle was administered by the physician at the end of the surgical procedure. The primary efficacy endpoint for the study was the proportion of patients with anterior chamber cell clearing (i.e., cell score=0) on postoperative day (POD) 8. The presence of anterior cells was assessed using a slit lamp binocular microscope up to 30 days post treatment. The percentage of patients with anterior chamber clearing at Day 8 was 20% in the placebo group, and 57%, and 60% in the 342 and 517 microgram treatment groups, respectively (Table 1). The percentage of subjects receiving rescue medication of ocular steroid or NSAID was significantly lower at Day 3, 8, 15 and 30 in the 342 and 517 microgram treatment groups compared to placebo (Table 2).

Table 1: Proportion of subjects with clearing of the anterior chamber cells by visit
 | Treatments |  |  | Difference and 97.5% CI
Visits | Placebo N=80 | DEX342 N=158 | DEX517 N=156 | DEX342 vs Placebo | DEX517 vs Placebo
Day 1 | 7 (9%) | 17 (11%) | 24 (15%) | 2% (-7%, 11%) | 7% (-3%, 16%)
Day 3 | 13 (16%) | 60 (38%) | 44 (28%) | 22% (9%, 34%) | 12% (0%, 24%)
Day 8 | 16 (20%) | 90 (57%) | 94 (60%) | 37% (24%, 50%) | 40% (27%, 54%)
Day 15 | 21 (26%) | 83 (52%) | 91 (58%) | 26% (12%, 40%) | 32% (18%, 46%)
Day 30 | 28 (35%) | 113 (72%) | 103 (66%) | 36% (22%, 51%) | 31% (16%, 46%)
Subjects who received rescue medication were treated as failure.

Table 2: Proportion of subjects receiving rescue medications
Visits | Number (Percent) of Patients Receiving Rescue Medication, and 95% CI
Visits | Placebo N=80 | DEX342 N=158 | DEX517 N=156
Day 1 | 10 (13%); 6%, 22% | 9 (6%); 3%, 10% | 10 (6%); 3%, 12%
Day 3 | 30 (38%); 27%, 49% | 9 (6%); 3%, 10% | 16 (10%); 6%,16%
Day 8 | 40 (50%); 39%, 61% | 12 (8%); 4%, 13% | 16 (10%); 6%,16%
Day 15 | 43 (54%); 42%, 65% | 22 (14%); 9%, 20% | 26 (17%); 11%, 24%
Day 30 | 43 (54%); 42%, 65% | 25 (16%); 10%, 22% | 31 (20%); 14%, 27%
Subjects who received an ocular corticosteroid or NSAID in study eye.

16 HOW SUPPLIED/STORAGE AND HANDLING

Each kit of DEXYCU contains a single dose for a single patient. The 2-mL glass vial is filled with 0.5 mL of 9% dexamethasone intraocular suspension and has a blue cap (NDC # 71879-001-01).

Each kit also contains one sterile 18-gauge, 1.5-inch needle with a plastic cap attached, one sterile plastic 1-mL syringe for withdrawal of the vial contents, one sterile 25-gauge 8-mm cannula with a plastic cap attached for the intraocular administration, and one syringe assembly pouch containing a sterile ring and a sterile syringe guide used for measuring and injection of the 0.005 mL dose.

STORAGE AND HANDLING

Store at 20°C to 25°C (68°F to 77°F).

Manufactured for: EyePoint Pharmaceuticals US, Inc. Watertown, MA 02472

Patented. See https://eyepointpharma.com/patent-notification/

PRINCIPAL DISPLAY PANEL - 0.005 mL Vial Carton

DEXYCU™
(dexamethasone intraocular suspension) 9%
0.005 mL dose in single dose vial
for intraocular administration

Please see enclosed full Prescribing Information for Instructions

Rx Only

NDC 71879-001-01

EYEPOINT™
PHARMACEUTICALS

For Intraocular Injection

Store at 20°C to 25°C (68°F to 77°F)